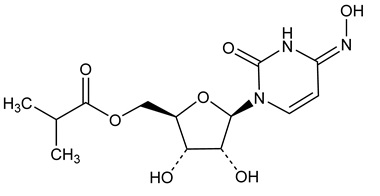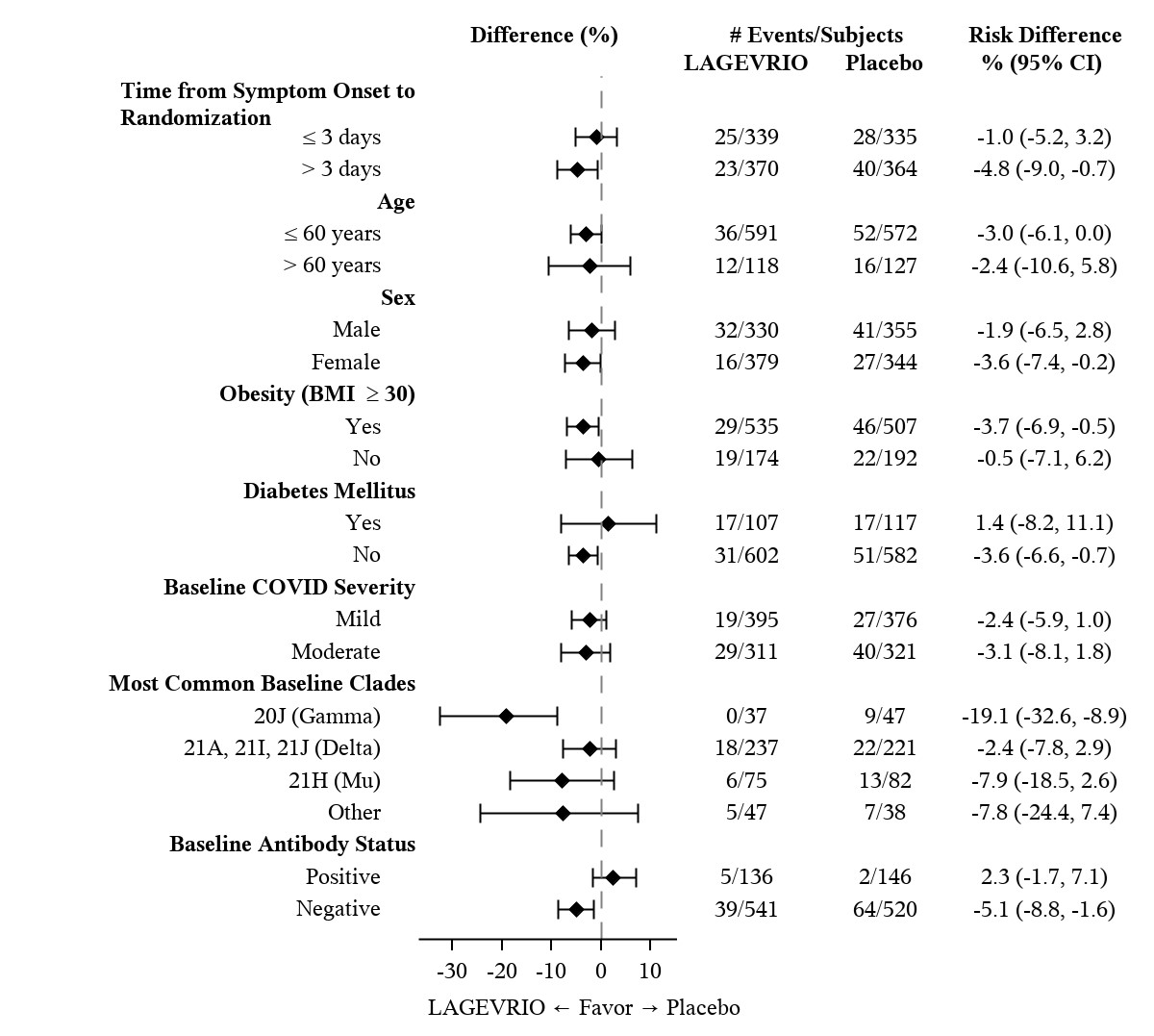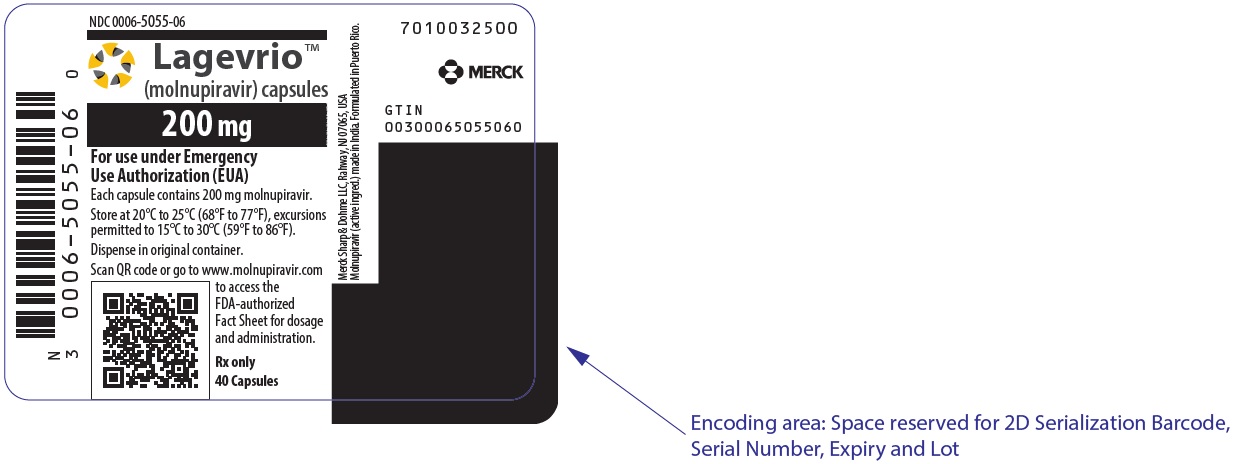 DRUG LABEL: LAGEVRIO
NDC: 0006-5055 | Form: CAPSULE
Manufacturer: Merck Sharp & Dohme LLC
Category: prescription | Type: HUMAN PRESCRIPTION DRUG LABEL
Date: 20250711

ACTIVE INGREDIENTS: MOLNUPIRAVIR 200 mg/1 1
INACTIVE INGREDIENTS: HYDROXYPROPYL CELLULOSE, UNSPECIFIED; MICROCRYSTALLINE CELLULOSE; CROSCARMELLOSE SODIUM; WATER; MAGNESIUM STEARATE; FERRIC OXIDE RED; TITANIUM DIOXIDE; HYPROMELLOSE, UNSPECIFIED

FACT SHEET FOR HEALTHCARE PROVIDERS: EMERGENCY USE AUTHORIZATION FOR LAGEVRIO™ (molnupiravir) CAPSULES

HIGHLIGHTS OF EMERGENCY USE AUTHORIZATION (EUA)
These highlights of the EUA do not include all the information needed to use LAGEVRIO under the EUA. See the FULL FACT SHEET FOR HEALTHCARE PROVIDERS for LAGEVRIO.
LAGEVRIO™ (molnupiravir) capsules, for oral use
Original EUA Authorized Date: 12/23/2021
Revised EUA Authorized Date: 06/2024

MANDATORY REQUIREMENTS FOR ADMINISTRATION OF LAGEVRIO UNDER EMERGENCY USE AUTHORIZATION
Refer to FULL FACTSHEET for details.

--------------RECENT MAJOR CHANGES-----------

Use in Specific Populations (Section 8.3), Nonclinical Toxicology (Section 13.1): Updated 06/2024

Dosage and Administration (Section 2.3): Addition of administration via gastrostomy and gastrojejunostomy feeding tubes 06/2024

Mandatory Requirements Box, Emergency Use Authorization (Section 1): Updated 10/2023

Limitations of Authorized Use (Section 1): Updated 10/2023

Adverse Reactions: Removal of Section 6.5 10/2023

Adverse Reactions (Section 6.2): update to post-authorization experience section 07/2023

------------EUA FOR LAGEVRIO-----------

The U.S. Food and Drug Administration (FDA) has issued an EUA for the emergency use of the unapproved LAGEVRIO, a nucleoside analogue that inhibits SARS-CoV-2 replication by viral mutagenesis for the treatment of adults with mild-to-moderate coronavirus disease 2019 (COVID-19):

- who are at high risk for progression to severe COVID-19, including hospitalization or death, and for
- whom alternative COVID-19 treatment options approved or authorized by FDA are not accessible or clinically appropriate.

LAGEVRIO is not FDA-approved for any use including for use for the treatment of COVID-19. Prior to initiating treatment with LAGEVRIO, carefully consider the known and potential risks and benefits. (1)

LIMITATIONS OF AUTHORIZED USE (1)

- LAGEVRIO is not authorized
  - for use in patients less than 18 years of age (5.3)
  - for initiation of treatment in patients requiring hospitalization due to COVID-19. Benefit of treatment with LAGEVRIO has not been observed in subjects when treatment was initiated after hospitalization due to COVID-19. (2.1)
  - for use for longer than 5 consecutive days.
  - for pre-exposure or post-exposure prophylaxis for prevention of COVID-19.

LAGEVRIO may only be prescribed for an individual patient by physicians, advanced practice registered nurses, and physician assistants that are licensed or authorized under state law to prescribe drugs in the therapeutic class to which LAGEVRIO belongs (i.e., anti-infectives).

LAGEVRIO is authorized only for the duration of the declaration that circumstances exist justifying the authorization of the emergency use of LAGEVRIO under section 564(b)(1) of the Act, 21 U.S.C. § 360bbb-3(b)(1), unless the authorization is terminated or revoked sooner.

See the box in the beginning of the Full Fact Sheet for details on mandatory requirements for administration of LAGEVRIO under emergency use authorization.

See Full Fact Sheet for Healthcare Providers for the justification for emergency use of drugs during the COVID-19 pandemic, information on available alternatives, and additional information on COVID-19.

------DOSAGE AND ADMINISTRATION------

- 800 mg (four 200 mg capsules) taken orally every 12 hours for 5 days, with or without food. (2.1, 2.3)
- Take LAGEVRIO as soon as possible after a diagnosis of COVID-19 has been made, and within 5 days of symptom onset. (2.1)
- Completion of the full 5-day treatment course and continued isolation in accordance with public health recommendations are important to maximize viral clearance and minimize transmission of SARS-CoV-2. (2.1)
- LAGEVRIO is not authorized for use for longer than 5 consecutive days because the safety and efficacy have not been established. (2.1)

-----DOSAGE FORMS AND STRENGTHS-----

Capsules: 200 mg (3)

------------CONTRAINDICATIONS------------

No contraindications have been identified based on the limited available data on the emergency use of LAGEVRIO authorized under this EUA. (4)

------WARNINGS AND PRECAUTIONS------

- Embryo-Fetal Toxicity: LAGEVRIO is not recommended for use during pregnancy. (5.1, 8.1, 8.3)
- Hypersensitivity reactions, including anaphylaxis have been reported with LAGEVRIO. If signs and symptoms of a clinically significant hypersensitivity reaction or anaphylaxis occur, immediately discontinue LAGEVRIO. (5.2)
- Bone and Cartilage Toxicity: LAGEVRIO is not authorized for use in patients less than 18 years of age because it may affect bone and cartilage growth. (5.3, 8.4, 13.2)

-----------ADVERSE REACTIONS-----------

Most common adverse reactions (incidence ≥ 1%) are diarrhea, nausea, and dizziness. (6.1)

You or your designee must report all SERIOUS ADVERSE EVENTS or MEDICATION ERRORS potentially related to LAGEVRIO (1) by submitting FDA Form 3500 online, (2) by downloading this form and then submitting by mail or fax, or (3) contacting the FDA at 1-800-FDA-1088 to request this form. Please also provide a copy of this form to Merck Sharp & Dohme LLC, Rahway, NJ USA at 1-800-672-6372 or Fax 215-616-5677 (6.4)

-------------DRUG INTERACTIONS--------------

No drug interactions have been identified based on the limited available data on the emergency use of LAGEVRIO authorized under this EUA. (7)

----------USE IN SPECIFIC POPULATIONS---------

- Pregnancy: The use of LAGEVRIO is not recommended during pregnancy. Advise individuals of childbearing potential to use effective contraception correctly and consistently, as applicable, for the duration of treatment and for 4 days after the last dose of LAGEVRIO. (8.1, 8.3)
- Lactation: Breastfeeding is not recommended during treatment and for 4 days after the last dose of LAGEVRIO. A lactating individual may consider interrupting breastfeeding and may consider pumping and discarding breast milk during treatment and for 4 days after the last dose of LAGEVRIO. (8.2)

See FACT SHEET FOR PATIENTS AND CAREGIVERS.

TABLE OF CONTENTS*

MANDATORY REQUIREMENTS FOR ADMINISTRATION OF LAGEVRIO UNDER EMERGENCY USE AUTHORIZATION

1 EMERGENCY USE AUTHORIZATION

2 DOSAGE AND ADMINISTRATION

2.1 Dosage for Emergency Use of LAGEVRIO in Adult Patients

2.2 Dosage Adjustments in Specific Populations

2.3 Administration via Nasogastric (NG), Orogastric (OG) and Gastrostomy (G) Tubes that are 12F or Larger or via Gastrojejunostomy (GJ) Tubes that are 14F or Larger

3 DOSAGE FORMS AND STRENGTHS

4 CONTRAINDICATIONS

5 WARNINGS AND PRECAUTIONS

5.1 Embryo-Fetal Toxicity

5.2 Hypersensitivity Including Anaphylaxis

5.3 Bone and Cartilage Toxicity

6 ADVERSE REACTIONS

6.1 Adverse Reactions from Clinical Studies

6.2 Post-Authorization Experience

6.4 Required Reporting for Serious Adverse Events and Medication Errors

7 DRUG INTERACTIONS

8 USE IN SPECIFIC POPULATIONS

8.1 Pregnancy

8.2 Lactation

8.3 Females and Males of Reproductive Potential

8.4 Pediatric Use

8.5 Geriatric Use

8.6 Renal Impairment

8.7 Hepatic Impairment

10 OVERDOSAGE

11 DESCRIPTION

12 CLINICAL PHARMACOLOGY

12.1 Mechanism of Action

12.2 Pharmacodynamics

12.3 Pharmacokinetics

12.4 Microbiology

13 NONCLINICAL TOXICOLOGY

13.1 Carcinogenesis, Mutagenesis, Impairment of Fertility

13.2 Animal Toxicology and/or Pharmacology

14 CLINICAL STUDIES

16 HOW SUPPLIED/STORAGE AND HANDLING

17 PATIENT COUNSELING INFORMATION

18 MANUFACTURER INFORMATION

* Sections or subsections omitted from the EUA are not listed

FULL FACT SHEET FOR HEALTHCARE PROVIDERS

BOXED WARNING

MANDATORY REQUIREMENTS FOR ADMINISTRATION OF LAGEVRIO UNDER EMERGENCY USE AUTHORIZATION

In order to mitigate the risks of using this unapproved product under the EUA and to optimize the potential benefit of LAGEVRIO, the following steps are required. Use of LAGEVRIO under this EUA is limited to the following (all requirements must be met):

1. Treatment of adults with mild-to-moderate COVID-19 who are at high risk for progression to severe COVID-19, including hospitalization or death and for whom alternative COVID-19 treatment options approved or authorized by FDA are not accessible or clinically appropriate [see Limitations of Authorized Use (1)].
2. As the prescribing healthcare provider, review the information contained within the “Fact Sheet for Patients and Caregivers” with your patient or caregiver prior to the patient receiving LAGEVRIO. Healthcare providers must provide the patient/caregiver with an electronic or hard copy of the “Fact Sheet for Patients and Caregivers” prior to the patient receiving LAGEVRIO and must document that the patient/caregiver has been given an electronic or hard copy of the “Fact Sheet for Patients and Caregivers”.
3. The prescribing healthcare providers must inform the patient/caregiver that:
  1. LAGEVRIO is an unapproved drug that is authorized for use under this Emergency Use Authorization.
  2. Other therapeutics are currently approved for the same use as LAGEVRIO [see Emergency Use Authorization (1) - Information Regarding Available Alternatives for the EUA Authorized Use].
  3. There are benefits and risks of taking LAGEVRIO as outlined in the “Fact Sheet for Patients and Caregivers.”
  4. There is a pregnancy registry.
  5. Females of childbearing potential should use a reliable method of contraception correctly and consistently, as applicable, for the duration of treatment and for 4 days after the last dose of LAGEVRIO.
  6. Males of reproductive potential who are sexually active with females of childbearing potential should use a reliable method of contraception correctly and consistently during treatment and for at least 3 months after the last dose.
4. The prescribing healthcare provider must assess whether a female of childbearing potential is pregnant or not, if clinically indicated [see Warnings and Precautions (5.1) and Use in Specific Populations (8.3)].
5. Based on findings from animal reproduction studies, LAGEVRIO may cause fetal harm when administered to pregnant individuals. If LAGEVRIO is used during pregnancy, prescribing healthcare providers must communicate to the patient the known and potential benefits and the potential risks of LAGEVRIO use during pregnancy, as outlined in the “Fact Sheet for Patients and Caregivers” [see Warnings and Precautions (5.1, 5.3), Use in Specific Populations (8.1, 8.3) and Nonclinical Toxicology (13.1)].
6. If the decision is made to use LAGEVRIO during pregnancy, the prescriber must document that the known and potential benefits and the potential risks of LAGEVRIO use during pregnancy, as outlined in the “Fact Sheet for Patients and Caregivers,” were discussed with the patient.
7. The prescribing healthcare provider must document that a pregnant individual was made aware of the pregnancy registry at https://covid-pr.pregistry.com or 1-800-616-3791.
8. The prescribing healthcare provider and/or the provider’s designee is/are responsible for mandatory reporting of all medication errors and serious adverse events potentially related to LAGEVRIO within 7 calendar days from the healthcare provider’s awareness of the event [see Adverse Reactions (6.4)].

For information on clinical studies of LAGEVRIO and other therapies for the treatment of COVID-19, see www.clinicaltrials.gov .

1 EMERGENCY USE AUTHORIZATION

The U.S. Food and Drug Administration (FDA) has issued an Emergency Use Authorization (EUA) to permit the emergency use of the unapproved product LAGEVRIO™ for treatment of adults with mild-to-moderate coronavirus disease 2019 (COVID-19):

- who are at high risk for progression to severe COVID-19, including hospitalization or death. Refer to CDC website [https://www.cdc.gov/coronavirus/2019-ncov/hcp/clinical-care/underlyingconditions.html . Healthcare providers should consider the benefit-risk for an individual patient.] for additional details, and for
- whom alternative COVID-19 treatment options approved or authorized by FDA are not accessible or clinically appropriate.

LIMITATIONS OF AUTHORIZED USE

- LAGEVRIO is not authorized for use in patients who are less than 18 years of age [see Warnings and Precautions (5.3)].
- LAGEVRIO is not authorized for initiation of treatment in patients hospitalized due to COVID-19 [Should a patient require hospitalization after starting treatment with LAGEVRIO, the patient may complete the full 5 day treatment course per the healthcare provider’s discretion.] . Benefit of treatment with LAGEVRIO has not been observed in subjects when treatment was initiated after hospitalization due to COVID-19 [see Dosing and Administration (2.1)].
- LAGEVRIO is not authorized for use for longer than 5 consecutive days.
- LAGEVRIO is not authorized for pre-exposure or post-exposure prophylaxis for prevention of COVID-19.

LAGEVRIO may only be prescribed for an individual patient by physicians, advanced practice registered nurses, and physician assistants that are licensed or authorized under state law to prescribe drugs in the therapeutic class to which LAGEVRIO belongs (i.e., anti-infectives).

LAGEVRIO is not approved for any use, including for use for the treatment of COVID-19.

Prior to initiating treatment with LAGEVRIO, carefully consider the known and potential risks and benefits [see Warnings and Precautions (5.1, 5.3), Use in Specific Populations (8.1, 8.3) and Nonclinical Toxicology (13.1)].

LAGEVRIO is authorized only for the duration of the declaration that circumstances exist justifying the authorization of the emergency use of LAGEVRIO under section 564(b)(1) of the Act, 21 U.S.C. § 360bbb-3(b)(1), unless the authorization is terminated or revoked sooner.

Justification for Emergency Use of Drugs During the COVID-19 Pandemic

There is currently an outbreak of Coronavirus Disease 2019 (COVID-19) caused by SARS-CoV-2, a novel coronavirus. The Secretary of HHS has:

- Determined that there is a public health emergency, or significant potential for a public health emergency, related to COVID-19 [See U.S. Department of Health and Human Services, Determination of a Public Health Emergency and Declaration that Circumstances Exist Justifying Authorizations Pursuant to Section 564(b) of the Federal Food, Drug, and Cosmetic Act, 21 U.S.C. § 360bbb-3. February 4, 2020; https://www.federalregister.gov/documents/2020/02/07/2020-02496/determination-of-public-health-emergency. See also U.S. Department of Health and Human Services, Amended Determination of a Public Health Emergency or Significant Potential for a Public Health Emergency Pursuant to Section 564(b) of the Federal Food, Drug, and Cosmetic Act, 21 U.S.C. § 360bbb-3(b). March 15, 2023 (“Amended Determination”); https://www.federalregister.gov/documents/2023/03/20/2023-05609/covid-19-emergency-use-authorization-declaration.] .
- Declared that circumstances exist justifying the authorization of emergency use of drugs and biological products for the prevention or treatment of COVID-19 [See U.S. Department of Health and Human Services, Declaration that Circumstances Exist Justifying Authorizations Pursuant to Section 564(b) of the Federal Food, Drug, and Cosmetic Act, 21 U.S.C. § 360bbb-3, 85 FR 18250 (April 1, 2020); https://www.federalregister.gov/documents/2020/04/01/2020-06905/emergency-use-authorization-declaration. See also Amended Determination (“The declarations issued pursuant to section 564(b)(1) of the FD&C Act that circumstances exist justifying the authorization of emergency use of certain in vitro diagnostics, personal respiratory protective devices, other medical devices and drugs and biological products, as set forth in those declarations, and that are based on the February 4, 2020 determination, remain in effect until those declarations are terminated in accordance with section 564 of the FD&C Act.”).] .

An EUA is a FDA authorization for the emergency use of an unapproved product or unapproved use of an approved product (i.e., drug, biological product, or device) in the United States under certain circumstances including, but not limited to, when the Secretary of HHS declares that there is a public health emergency that affects the national security or the health and security of United States citizens living abroad, and that involves biological agent(s) or a disease or condition that may be attributable to such agent(s). Criteria for issuing an EUA include:

- The biological agent(s) can cause a serious or life-threatening disease or condition;
- Based on the totality of the available scientific evidence (including data from adequate and well-controlled clinical trials, if available), it is reasonable to believe that
  - the product may be effective in diagnosing, treating, or preventing the serious or life-threatening disease or condition; and
  - the known and potential benefits of the product - when used to diagnose, prevent, or treat such disease or condition - outweigh the known and potential risks of the product, taking into consideration the material threat posed by the biological agent(s);
- There is no adequate, approved, and available alternative to the product for diagnosing, preventing, or treating the serious or life-threatening disease or condition.

APPROVED AVAILABLE ALTERNATIVES

Veklury (remdesivir) is FDA-approved for the treatment of COVID-19 in adults and pediatric patients (at least 28 days old and weighing at least 3 kg) who are not hospitalized and have mild-to-moderate COVID-19, and who are at high risk for progression to severe COVID-19, including hospitalization or death. Veklury is administered via intravenous infusion for a total treatment duration of 3 days.

Although Veklury is an approved alternative to LAGEVRIO for the treatment of mild-to-moderate COVID-19 in adults and who are at high risk for progression to severe COVID-19, including hospitalization or death, FDA does not consider Veklury to be an adequate alternative to LAGEVRIO for this authorized use because it may not be feasible or clinically appropriate for certain patients (e.g., it requires a 3-day intravenous treatment duration).

Paxlovid (nirmatrelvir tablets; ritonavir tablets co-packaged for oral use) is FDA-approved for the treatment of mild-to-moderate COVID-19 in adults who are at high risk for progression to severe COVID-19, including hospitalization or death. Paxlovid is administered orally for a total treatment duration of 5 days. Although Paxlovid is an approved alternative to LAGEVRIO for the treatment of mild-to-moderate COVID-19 in adults and who are at high risk for progression to severe COVID-19, including hospitalization or death, FDA does not consider Paxlovid to be an adequate alternative to LAGEVRIO for this authorized use because it may not be clinically appropriate for patients on medications that are primarily metabolized by CYP3A and/or that are strong CYP3A inducers.

For additional information on all products authorized for treatment or prevention of COVID-19, please see https://www.fda.gov/emergency-preparedness-and-response/mcm-legal-regulatory-and-policy-framework/emergency-use-authorization .

For information on clinical studies of LAGEVRIO and other therapies for the treatment of COVID-19, see www.clinicaltrials.gov.

2 DOSAGE AND ADMINISTRATION

2.1 Dosage for Emergency Use of LAGEVRIO in Adult Patients

The dosage in adult patients is 800 mg (four 200 mg capsules) taken orally every 12 hours for 5 days, with or without food [see Clinical Pharmacology (12.3)]. Take LAGEVRIO as soon as possible after a diagnosis of COVID-19 has been made, and within 5 days of symptom onset [see Emergency Use Authorization (1) and Clinical Studies (14)].

Completion of the full 5-day treatment course and continued isolation in accordance with public health recommendations are important to maximize viral clearance and minimize transmission of SARS-CoV-2 [see Patient Counseling Information (17)].

LAGEVRIO is not authorized for use for longer than 5 consecutive days because the safety and efficacy have not been established.

If the patient misses a dose of LAGEVRIO within 10 hours of the time it is usually taken, the patient should take it as soon as possible and resume the normal dosing schedule. If the patient misses a dose by more than 10 hours, the patient should not take the missed dose and instead take the next dose at the regularly scheduled time. The patient should not double the dose to make up for a missed dose.

Should a patient require hospitalization after starting treatment with LAGEVRIO, the patient may complete the full 5 day treatment course per the healthcare provider’s discretion.

2.2 Dosage Adjustments in Specific Populations

No dosage adjustment is recommended based on renal or hepatic impairment or in geriatric patients [see Use in Specific Populations (8.5, 8.6, 8.7)].

2.3 Administration via Nasogastric (NG), Orogastric (OG) and Gastrostomy (G) Tubes that are 12F or Larger or via Gastrojejunostomy (GJ) Tubes that are 14F or Larger

1. Open four (4) capsules and transfer contents into a clean container with a lid.
2. Add 40 mL of water to the container.
3. Put the lid on the container and shake to mix the capsule contents and water thoroughly for 3 minutes.
  - NOTE: Capsule contents may not dissolve completely.
  - The prepared mixture may have visible undissolved particulates and are acceptable for administration.
4. Flush the tube with 5 mL of water prior to administration.
5. Using an appropriate syringe, draw up the entire contents from the container and administer immediately through the tube. If using a GJ tube, administer through the gastric port. Do not keep the mixture for future use.
6. If any portion of the capsule contents are left in the container, add 10 mL of water to the container, mix, and using the same syringe draw up the entire contents of the container and administer through the tube. Repeat as needed until no capsule contents are left in the container or syringe.
7. Flush the tube with 5 mL of water twice (10 mL total) after administration of the mixture.

3 DOSAGE FORMS AND STRENGTHS

Capsules: 200 mg, Swedish Orange opaque size 0 capsules. The capsules have the corporate logo and “82” printed in white ink.

4 CONTRAINDICATIONS

No contraindications have been identified based on the limited available data on the emergency use of LAGEVRIO authorized under this EUA.

5 WARNINGS AND PRECAUTIONS

There are limited clinical data available for LAGEVRIO. Serious and unexpected adverse events may occur that have not been previously reported with LAGEVRIO use.

5.1 Embryo-Fetal Toxicity

Based on findings from animal reproduction studies, LAGEVRIO may cause fetal harm when administered to pregnant individuals. There are no available human data on the use of LAGEVRIO in pregnant individuals to evaluate the risk of major birth defects, miscarriage or adverse maternal or fetal outcomes; therefore, LAGEVRIO is not recommended for use during pregnancy. When considering LAGEVRIO for a pregnant individual, the prescribing healthcare provider must communicate the known and potential benefits and the potential risks of using LAGEVRIO during pregnancy to the pregnant individual. LAGEVRIO is authorized to be prescribed to a pregnant individual only after the healthcare provider has determined that the benefits would outweigh the risks for that individual patient. If the decision is made to use LAGEVRIO during pregnancy, the prescribing healthcare provider must document that the known and potential benefits and the potential risks of using LAGEVRIO during pregnancy were communicated to the pregnant individual.

Advise individuals of childbearing potential of the potential risk to a fetus and to use an effective method of contraception correctly and consistently, as applicable, during treatment with LAGEVRIO and for 4 days after the final dose [see Use in Specific Populations (8.1, 8.3 and Nonclinical Toxicology (13.1)].

Prior to initiating treatment with LAGEVRIO, assess whether an individual of childbearing potential is pregnant or not, if clinically indicated. Pregnancy status does not need to be confirmed in patients who have undergone permanent sterilization, are currently using an intrauterine system or contraceptive implant, or in whom pregnancy is not possible. In all other patients, assess whether the patient is pregnant based on the first day of last menstrual period in individuals who have regular menstrual cycles, is using a reliable method of contraception correctly and consistently or have had a negative pregnancy test. A pregnancy test is recommended if the individual has irregular menstrual cycles, is unsure of the first day of last menstrual period or is not using effective contraception correctly and consistently [see Box].

5.2 Hypersensitivity Including Anaphylaxis

Hypersensitivity reactions, including anaphylaxis, have been reported with LAGEVRIO. If signs and symptoms of a clinically significant hypersensitivity reaction or anaphylaxis occur, immediately discontinue LAGEVRIO and initiate appropriate medications and/or supportive care.

5.3 Bone and Cartilage Toxicity

LAGEVRIO is not authorized for use in patients less than 18 years of age because it may affect bone and cartilage growth. Bone and cartilage toxicity was observed in rats after repeated dosing [see Nonclinical Toxicity (13.2)]. The safety and efficacy of LAGEVRIO have not been established in pediatric patients [see Use in Specific Populations (8.4)].

6 ADVERSE REACTIONS

6.1 Adverse Reactions from Clinical Studies

The following adverse reactions have been observed in the clinical study of LAGEVRIO that supported the EUA. The adverse reaction rates observed in these clinical trials cannot be directly compared to rates in the clinical trials of another drug and may not reflect the rates observed in practice. Additional adverse events associated with LAGEVRIO may become apparent with more widespread use.

Overall, more than 900 subjects have been exposed to LAGEVRIO 800 mg twice daily in clinical trials. The safety assessment of LAGEVRIO is primarily based on an analysis from subjects followed through Day 29 in the Phase 3 study in non-hospitalized subjects with COVID-19 (MOVe-OUT) [see Clinical Studies (14)].

The safety of LAGEVRIO was evaluated based on an analysis of a Phase 3 double-blind trial (MOVe-OUT) in which 1,411 non-hospitalized subjects with COVID-19 were randomized and treated with LAGEVRIO (N=710) or placebo (N=701) for up to 5 days. Adverse events were those reported while subjects were on study intervention or within 14 days of study intervention completion/discontinuation.

Discontinuation of study intervention due to an adverse event occurred in 1% of subjects receiving LAGEVRIO and 3% of subjects receiving placebo. Serious adverse events occurred in 7% of subjects receiving LAGEVRIO and 10% receiving placebo; most serious adverse events were COVID-19 related. Adverse events leading to death occurred in 2 (<1%) subjects receiving LAGEVRIO and 12 (2%) of subjects receiving placebo.

The most common adverse reactions in the LAGEVRIO treatment group in MOVe-OUT are presented in Table 1, all of which were Grade 1 (mild) or Grade 2 (moderate).

Table 1: Adverse Reactions Occurring in Greater Than or Equal to 1% of Subjects Receiving LAGEVRIO in MOVe-OUT [Frequencies of adverse reactions are based on all adverse events attributed to study intervention by the investigator.]
 | LAGEVRIO N=710 | Placebo N=701
Diarrhea | 2% | 2%
Nausea | 1% | 1%
Dizziness | 1% | 1%

Laboratory Abnormalities

Selected Grade 3 and 4 laboratory abnormalities in chemistry (alanine aminotransferase, aspartate aminotransferase, creatinine, and lipase) and hematology (hemoglobin, platelets, and leukocytes) parameters all occurred at a rate of less than or equal to 2% and occurred at a similar rate across arms in MOVe-OUT.

6.2 Post-Authorization Experience

The following adverse reactions have been identified during post-authorization use of LAGEVRIO. Because these reactions are reported voluntarily from a population of uncertain size, it is not always possible to reliably estimate their frequency or establish a causal relationship to drug exposure.

Gastrointestinal Disorders

vomiting

Immune System Disorders

hypersensitivity, anaphylaxis, angioedema [see Warnings and Precautions (5.2)]

Skin and Subcutaneous Tissue Disorders

erythema, pruritus, rash, urticaria

6.4 Required Reporting for Serious Adverse Events and Medication Errors

The prescribing healthcare provider and/or the provider’s designee is/are responsible for mandatory reporting of all serious adverse events* and medication errors potentially related to LAGEVRIO within 7 calendar days from the healthcare provider’s awareness of the event, using FDA Form 3500 (for information on how to access this form, see below). The FDA requires that such reports, using FDA Form 3500, include the following:

- Patient demographics and baseline characteristics (e.g., patient identifier, age or date of birth, gender, weight, ethnicity, and race)
- A statement "LAGEVRIO use for COVID-19 under Emergency Use Authorization (EUA)” under the “Describe Event, Problem, or Product Use/Medication Error” heading
- Information about the serious adverse event or medication error (e.g., signs and symptoms, test/laboratory data, complications, timing of drug initiation in relation to the occurrence of the event, duration of the event, treatments required to mitigate the event, evidence of event improvement/disappearance after stopping or reducing the dosage, evidence of event reappearance after reintroduction, clinical outcomes).
- Patient’s preexisting medical conditions and use of concomitant products
- Information about the product (e.g., dosage, route of administration, NDC #).

Submit adverse event and medication error reports, using Form 3500, to FDA MedWatch using one of the following methods:

- Complete and submit the report online: www.fda.gov/medwatch/report.htm
- Complete and submit a postage-paid FDA Form 3500 (https://www.fda.gov/media/76299/download) and return by:
  - Mail to MedWatch, 5600 Fishers Lane, Rockville, MD 20852-9787, or
  - Fax to 1-800-FDA-0178, or
- Call 1-800-FDA-1088 to request a reporting form

In addition, please provide a copy of all FDA MedWatch forms to:
Merck Sharp & Dohme LLC, Rahway, NJ USA
Fax: 215-616-5677
E-mail: dpoc.usa@msd.com

The prescribing healthcare provider and/or the provider’s designee is/are responsible for mandatory responses to requests from FDA for information about adverse events and medication errors following receipt of LAGEVRIO.

*Serious adverse events are defined as:

- Death;
- A life-threatening adverse event;
- Inpatient hospitalization or prolongation of existing hospitalization;
- A persistent or significant incapacity or substantial disruption of the ability to conduct normal life functions;
- A congenital anomaly/birth defect;
- Other important medical event, which may require a medical or surgical intervention to prevent death, a life-threatening event, hospitalization, disability, or congenital anomaly.

7 DRUG INTERACTIONS

No drug interactions have been identified based on the limited available data on the emergency use of LAGEVRIO authorized under this EUA. No clinical drug-drug interaction trials of LAGEVRIO with concomitant medications, including other treatments for mild-to-moderate COVID-19, have been conducted [see Clinical Pharmacology (12.3)].

8 USE IN SPECIFIC POPULATIONS

8.1 Pregnancy

Pregnancy Registry

There is a pregnancy registry that monitors pregnancy outcomes in individuals exposed to LAGEVRIO during pregnancy. The prescribing healthcare provider must document that a pregnant individual was made aware of the pregnancy registry at https://covid-pr.pregistry.com or 1-800-616-3791. Pregnant individuals exposed to LAGEVRIO or their healthcare providers can also report the exposure by contacting Merck Sharp & Dohme LLC, Rahway, NJ USA at 1-877-888-4231.

Risk Summary

Based on animal data, LAGEVRIO may cause fetal harm when administered to pregnant individuals. There are no available human data on the use of LAGEVRIO in pregnant individuals to evaluate the risk of major birth defects, miscarriage or adverse maternal or fetal outcomes; therefore, LAGEVRIO is not recommended during pregnancy [see Box and Warnings and Precautions (5.1)]. In an animal reproduction study, oral administration of molnupiravir to pregnant rats during the period of organogenesis resulted in embryofetal lethality and teratogenicity at 8 times the human NHC (N4-hydroxycytidine) exposures at the recommended human dose (RHD) and reduced fetal growth at ≥ 3 times the human NHC exposure at the RHD. Oral administration of molnupiravir to pregnant rabbits during the period of organogenesis resulted in reduced fetal body weights at 18 times the human NHC exposure at the RHD (see Data). When considering LAGEVRIO for a pregnant individual, the prescribing healthcare provider must communicate the known and potential benefits and the potential risks of using LAGEVRIO during pregnancy to the pregnant individual. LAGEVRIO may only be prescribed to a pregnant individual after the prescribing healthcare provider has determined that the benefits would outweigh the risks for that individual patient. If the decision is made to use LAGEVRIO during pregnancy, the prescribing healthcare provider must document that the known and potential benefits and potential risks of using LAGEVRIO during pregnancy were communicated to the pregnant individual [see Box]. There are maternal and fetal risks associated with untreated COVID-19 in pregnancy (see Clinical Considerations).

The estimated background risk of major birth defects and miscarriage for the indicated population is unknown. All pregnancies have a background risk of birth defect, loss, or other adverse outcomes. In the U.S. general population, the estimated background risk of major birth defects and miscarriage in clinically recognized pregnancies is 2 to 4% and 15 to 20%, respectively.

Clinical Considerations

Disease-associated maternal and/or embryo/fetal risk

COVID-19 in pregnancy is associated with adverse maternal and fetal outcomes, including preeclampsia, eclampsia, preterm birth, premature rupture of membranes, venous thromboembolic disease, and fetal death.

Data

Animal Data

In an embryofetal development (EFD) study in rats, molnupiravir was administered orally to pregnant rats at 0, 100, 250, or 500 mg/kg/day from gestation days (GDs) 6 to 17. Molnupiravir was also administered orally to pregnant rats at up to 1,000 mg/kg/day from GDs 6 to 17 in a preliminary EFD study. Developmental toxicities included post-implantation losses, malformations of the eye, kidney, and axial skeleton, and rib variations at 1,000 mg/kg/day (8 times the human NHC exposure at the RHD) and decreased fetal body weights and delayed ossification at ≥500 mg/kg/day (3 times the human NHC exposure at the RHD). There were no developmental toxicities at ≤250 mg/kg/day (less than the human NHC exposure at the RHD). Maternal toxicities included decreased food consumption and body weight losses, resulting in the early sacrifice of two of sixteen animals at 1,000 mg/kg/day, and decreased body weight gain at 500 mg/kg/day.

In an EFD study in rabbits, molnupiravir was administered orally to pregnant rabbits at 0, 125, 400, or 750 mg/kg/day from GDs 7 to 19. Developmental toxicity was limited to reduced fetal body weights at 750 mg/kg/day (18 times the human NHC exposures at the RHD). There was no developmental toxicity at ≤400 mg/kg/day (7 times the human NHC exposures at the RHD). Maternal toxicities included reduced food consumption and body weight gains, and abnormal fecal output at 750 mg/kg/day.

In a pre- and post-natal developmental study, molnupiravir was administered orally to female rats at doses up to 500 mg/kg/day (similar to the human NHC exposure at the RHD) from GD6 through lactation day 20. No effects were observed in offspring.

8.2 Lactation

Risk Summary

There are no data on the presence of molnupiravir or its metabolites in human milk. NHC was detected in the plasma of nursing pups from lactating rats administered molnupiravir (see Data). It is unknown whether molnupiravir has an effect on the breastfed infant or effects on milk production.

Based on the potential for adverse reactions in the infant from LAGEVRIO, breastfeeding is not recommended during treatment with LAGEVRIO and for 4 days after the final dose. A lactating individual may consider interrupting breastfeeding and may consider pumping and discarding breast milk during treatment and for 4 days after the last dose of LAGEVRIO [see Warnings and Precautions (5.1, 5.3)].

Data

When molnupiravir was administered to lactating rats at ≥250 mg/kg/day in the pre- and post-natal development study, NHC was detected in plasma of nursing pups.

8.3 Females and Males of Reproductive Potential

Based on animal studies, LAGEVRIO may cause fetal harm when administered to a pregnant individual.

Pregnancy Testing

Prior to initiating treatment with LAGEVRIO, assess whether an individual of childbearing potential is pregnant or not, if clinically indicated [see Warnings and Precautions (5.1)].

Contraception

Females

Advise individuals of childbearing potential to use a reliable method of contraception correctly and consistently, as applicable for the duration of treatment and for 4 days after the last dose of LAGEVRIO [see Warnings and Precautions (5.1)].

Males

While the risk is regarded as low, there is a theoretical risk for LAGEVRIO to affect offspring of treated males based on its mechanism of action. Advise sexually active individuals with partners of childbearing potential to use a reliable method of contraception correctly and consistently during treatment and for at least 3 months after the last dose of LAGEVRIO.
The risk beyond three months after the last dose of LAGEVRIO is unknown.

Molnupiravir was equivocal (neither clearly positive nor negative) in one in vivo mutagenicity assay of reticulocytes and RBCs which are used to reflect prior effects on hematopoietic stem cells in bone marrow. Molnupiravir was not mutagenic when assessed in in vivo assays of liver (somatic cells), bone marrow (somatic cells and stem cells), and sperm (male germ cells) from transgenic rats administered molnupiravir for 28 days [see Nonclinical Toxicology (13.1)].

8.4 Pediatric Use

LAGEVRIO is not authorized for use in patients less than 18 years of age.
Bone and cartilage toxicity were observed in a 3-month, repeat-dose toxicology study in rats. The safety and efficacy of LAGEVRIO have not been established in pediatric patients [see Warnings and Precautions (5.3) and Nonclinical Toxicology (13.2)].

8.5 Geriatric Use

In MOVe-OUT, there was no difference in safety and tolerability between patients ≥65 years of age and younger patients who were treated with LAGEVRIO. No dosage adjustment is recommended based on age. The PK of NHC was similar in geriatric patients compared to younger patients [see Clinical Pharmacology (12.3)].

8.6 Renal Impairment

No dosage adjustment in patients with any degree of renal impairment is recommended. Renal clearance is not a meaningful route of elimination for NHC. Mild or moderate renal impairment did not have a meaningful impact on the PK of NHC. While the PK of NHC has not been evaluated in patients with eGFR less than 30 mL/min/1.73m^2 or on dialysis, severe renal impairment, and end-stage renal disease (ESRD) are not expected to have a significant effect on NHC exposure [see Clinical Pharmacology (12.3)].

8.7 Hepatic Impairment

No dosage adjustment in patients with hepatic impairment is recommended. Preclinical data indicate that hepatic elimination is not expected to be a major route of NHC elimination therefore, hepatic impairment is unlikely to affect NHC exposure [see Clinical Pharmacology (12.3)].

10 OVERDOSAGE

There is no human experience of overdosage with LAGEVRIO. Treatment of overdose with LAGEVRIO should consist of general supportive measures including the monitoring of the clinical status of the patient. Hemodialysis is not expected to result in effective elimination of NHC.

11 DESCRIPTION

LAGEVRIO capsules contain molnupiravir, a nucleoside analogue that inhibits SARS-CoV-2 replication by viral mutagenesis and is the 5´-isobutyrate ester of the ribonucleoside analog N4-hydroxycytidine (NHC).

The chemical name for molnupiravir is {(2R,3S,4R,5R)-3,4-Dihydroxy-5-[(4Z)-4-(hydroxyimino)-2-oxo-3,4-dihydropyrimidin-1(2H)-yl]oxolan-2-yl}methyl 2-methylpropanoate. It has an empirical formula of C13H19N3O7 and its molecular weight is 329.31 g/mol. Its structural formula is:

Molnupiravir is a white to off-white powder that is soluble in water.

Each LAGEVRIO capsule, for oral use, contains 200 mg of molnupiravir and the following inactive ingredients: croscarmellose sodium, hydroxypropyl cellulose, magnesium stearate and microcrystalline cellulose and purified water. The capsule shell is made of hypromellose, red iron oxide and titanium dioxide. The capsule is printed with white ink made of butyl alcohol, dehydrated alcohol, isopropyl alcohol, potassium hydroxide, propylene glycol, purified water, shellac, strong ammonia solution and titanium dioxide.

12 CLINICAL PHARMACOLOGY

12.1 Mechanism of Action

Molnupiravir is a prodrug with antiviral activity against SARS-CoV-2. It is metabolized to the cytidine nucleoside analogue, NHC which distributes into cells where NHC is phosphorylated to form the pharmacologically active ribonucleoside triphosphate (NHC-TP). NHC-TP incorporation (as NHC-monophosphate [NHC-MP]) into SARS-CoV-2 RNA by the viral RNA polymerase (nsp12) results in an accumulation of errors in the viral genome leading to inhibition of replication. The mechanism of action (known as viral error catastrophe or viral lethal mutagenesis) is supported by biochemical and cell culture data, studies of SARS-CoV-2 infection in animal models, and analyses of SARS-CoV-2 genome sequences in human subjects treated with LAGEVRIO.

12.2 Pharmacodynamics

The relationship between NHC and intracellular NHC-TP with antiviral efficacy has not been evaluated clinically.

12.3 Pharmacokinetics

Molnupiravir is a 5´-isobutyrate prodrug of NHC that is hydrolyzed during or after absorption. NHC, the primary circulating analyte, is taken up by cells and anabolized to NHC-TP. NHC is eliminated by metabolism to uridine and/or cytidine through the same pathways involved in endogenous pyrimidine metabolism. NHC pharmacokinetics are shown in Table 2.

Plasma NHC concentrations in patients (N=5) following administration of molnupiravir via nasogastric or orogastric tube fell within the range of NHC concentrations following oral molnupiravir capsule administration under the same dosing regimen.

Table 2: Pharmacokinetics of NHC After Multiple Oral Administration of 800 mg LAGEVRIO Every 12 Hours
 | NHC Geometric Mean (%CV)
Pharmacokinetics in Patients
AUC0-12hr (ng*hr/mL) [Values were obtained from population PK analysis.] | 8260 (41.0)
Cmax (ng/mL) | 2330 (36.9)
C12hr (ng/mL) | 31.1 (124)
Pharmacokinetics in Healthy Subjects
AUC0-12hr (ng*hr/mL) | 8330 (17.9)
Cmax (ng/mL) | 2970 (16.8)
C12hr (ng/mL) | 16.7 (42.8)
AUC Accumulation Ratio | 1.09 (11.8)
Absorption
Tmax (hr) [Median [min - max]] | 1.50 [1.00 – 2.02]
Effect of Food | 35% reduction in Cmax, no effect on AUC
Distribution
Plasma Protein Binding (in vitro) | 0%
Apparent Volume of Distribution (L) | 142
Elimination
Effective t1/2 (hr) | 3.3
Apparent Clearance (L/hr) | 76.9
Fraction of dose excreted in urine over the time interval of 0-12 hours | 3% (81.6%)
Values were obtained from a Phase 1 study of healthy subjects, unless otherwise indicated.

Specific Populations

Population PK analysis results indicated that age, sex, race, ethnicity, or disease severity do not meaningfully influence the PK of NHC.

Pediatric Patients

LAGEVRIO has not been studied in pediatric patients.

Patients with Renal Impairment

Renal clearance is not a meaningful route of elimination for NHC. In a population PK analysis, mild or moderate renal impairment did not have a meaningful impact on the PK of NHC. The PK of molnupiravir and NHC has not been evaluated in patients with eGFR less than 30 mL/min/1.73m^2 or on dialysis.

Patients with Hepatic Impairment

The PK of molnupiravir and NHC has not been evaluated in patients with moderate and severe hepatic impairment. Preclinical data indicate that hepatic elimination is not expected to be a major route of NHC elimination; therefore, hepatic impairment is unlikely to affect NHC exposure.

Drug Interaction Studies

In vitro study results indicated that molnupiravir and NHC are not substrates of CYP enzymes or human P-gp and BCRP transporters. In vitro study results also indicated that molnupiravir and NHC are not inhibitors of CYP1A2, 2B6, 2C8, 2C9, 2C19, 2D6, and 3A4 or inhibitors of OATP1B1, OATP1B3, OCT1, OCT2, OAT1, OAT3, MATE1, MATE2K, MRP2, MDR1 and BCRP or inducers of CYP1A2, 2B6, and 3A4. The interaction between molnupiravir with concomitant medications, including other treatments for mild-to-moderate COVID-19, has not been evaluated.

12.4 Microbiology

Antiviral Activity

NHC, the nucleoside analogue metabolite of molnupiravir, was active in cell culture assays against SARS-CoV-2 (USA-WA1/2020 isolate) with 50% effective concentrations (EC50 values) ranging between 0.67 to 2.7 µM in A-549 cells and 0.32 to 2.0 µM in Vero E6 cells. NHC had similar antiviral activity against SARS-CoV-2 variants Alpha (B.1.1.7), Beta (B.1.351), Gamma (P.1), Delta (B.1.617.2), Lambda (C.37), Mu (B.1.621) and Omicron (B.1.1.529/BA.1, BA.1.1, BA.2, BA.4 and BA.5), with mean EC50 values of 0.55-3.0 μM. NHC had non-antagonistic antiviral activity with remdesivir against SARS-CoV-2 in cell culture.

Resistance

No amino acid substitutions in SARS-CoV-2 associated with resistance to NHC have been identified in Phase 2 clinical trials evaluating LAGEVRIO for the treatment of COVID-19. Studies to evaluate selection of resistance to NHC with SARS-CoV-2 in cell culture have not been completed. Resistance selection studies have been conducted with other coronaviruses (MHV and MERS-CoV) and showed a low likelihood of resistance development to NHC. Following 30 passages in cell culture, only a 2-fold decrease in susceptibility was observed and no NHC resistance-associated amino acid substitutions were identified.

In clinical trials, encoded amino acid changes (substitutions, deletions or insertions) were more likely to be detected in viral sequences in subjects treated with LAGEVRIO compared to placebo. In a small number of subjects amino acid changes in the spike protein occurred at positions targeted by monoclonal antibodies and vaccines. The clinical and public health significance of these changes are unknown.

Cross-Resistance

NHC retained activity in cell culture against virus with polymerase (nsp 12) substitutions (e.g., F480L, V557L and E802D) associated with decreased remdesivir susceptibility, indicating a lack of cross-resistance.

Activity against SARS-CoV-2 in animal models

The antiviral activity of molnupiravir has been demonstrated in mouse, hamster, and ferret models of SARS-CoV-2 infection when dosing was administered prior to or within 1-2 days after viral challenge. In SARS-CoV-2 infected ferrets, molnupiravir significantly reduced SARS-CoV-2 viral titers in the upper respiratory tract and completely inhibited viral spread to untreated contact animals. In SARS-CoV-2 infected Syrian hamsters, molnupiravir reduced viral RNA and infectious virus titers in the lungs of animals. Histopathological analysis of lung tissue harvested after infection showed significantly reduced SARS-CoV-2 viral antigen levels and a lower abundance of pulmonary lesions in molnupiravir-treated animals compared with controls.

In Vitro Cytotoxicity

NHC, the nucleoside analogue metabolite of molnupiravir, had variable cytotoxicity against different mammalian cell types with CC50 values ranging from 7.5 µM (human lymphoid CEM cell line) to >100 µM, in 3-day exposure assays. Molnupiravir inhibited the proliferation of human bone marrow progenitor cells with CC50 values of 24.9 µM and 7.7 µM for erythroid and myeloid progenitor proliferation, respectively, in 14-day colony formation assays.

Viral RNA Rebound

Post-treatment increases in SARS-CoV-2 RNA shedding levels (i.e., viral RNA rebound) in nasopharyngeal samples were observed on Day 10, Day 15, and/or Day 29 in a subset of LAGEVRIO and placebo recipients in the Phase 3 MOVe-OUT trial. Approximately 1% of both LAGEVRIO and placebo recipients had evidence of recurrent COVID-19 symptoms coinciding with a rebound in viral RNA levels in nasopharyngeal samples.

Post-treatment viral RNA rebound was not associated with the primary clinical outcome of hospitalization or death through Day 29 following the single 5-day course of LAGEVRIO treatment. Post-treatment viral RNA rebound also was not associated with the detection of cell culture infectious virus in nasopharyngeal swab samples.

13 NONCLINICAL TOXICOLOGY

13.1 Carcinogenesis, Mutagenesis, Impairment of Fertility

Carcinogenesis

Molnupiravir was not carcinogenic in a 6-month oral carcinogenicity study in RasH2 transgenic (Tg.RasH2) mice at any dose tested (30, 100 or 300 mg/kg/day).

Mutagenesis

Molnupiravir and NHC were positive in the in vitro bacterial reverse mutation assay (Ames assay) with and without metabolic activation. Molnupiravir was studied in two in vivo rodent mutagenicity models. The in vivo Pig-a mutagenicity assay gave equivocal results. Molnupiravir was negative in in vivo Big Blue® (cII Locus) transgenic rodent mutagenicity assays in somatic and germ cells. Molnupiravir was negative for induction of chromosomal damage in in vitro micronucleus (with and without metabolic activation) and in vivo rat micronucleus assays.

Based on the totality of the available genotoxicity data and the duration of treatment (5 days), molnupiravir is low risk for genotoxicity.

Impairment of Fertility

There were no effects on fertility, mating performance or early embryonic development when molnupiravir was administered to female or male rats at NHC exposures approximately 2 and 6 times, respectively, the human NHC exposure at the RHD.

13.2 Animal Toxicology and/or Pharmacology

Bone and cartilage toxicity changes resulting in impaired transformation of growth cartilage into new bone were observed in the femur and tibia of rats in a 3-month toxicity study at ≥ 500 mg/kg/day (5 times the human NHC exposure at the RHD). There was no bone or cartilage toxicity in a 1-month toxicity study in rats up to 500 mg/kg/day (4 and 8 times the human NHC exposure at the RHD in females and males, respectively), in dogs dosed for 14 days up to 50 mg/kg/day (similar to the human NHC exposure at the RHD), or in a 1-month toxicity study in mice up to 2,000 mg/kg/day (19 times the human NHC exposure at the RHD).

Growth cartilage is not present in mature skeletons, therefore the bone and cartilage findings are not relevant for adult humans but may be relevant for pediatric patients [see Warnings and Precautions (5.3) and Use in Specific Populations (8.4)].

Reversible, dose-related bone marrow toxicity affecting all hematopoietic cell lines was observed in dogs at ≥17 mg/kg/day (less than the human NHC exposure at the RHD). Mild decreases in peripheral blood cell and platelet counts were seen after 7 days of molnupiravir treatment progressing to more severe hematological changes after 14 days of treatment. Neither bone marrow nor hematological toxicity was observed in a 1-month toxicity study in mice up to 2,000 mg/kg/day (19 times the human NHC exposure at the RHD) and a 3-month toxicity study in rats up to 1,000 mg/kg/day (9 and 15 times the human NHC exposure at the RHD in females and males, respectively).

14 CLINICAL STUDIES

Clinical data supporting this EUA are based on data from 1,433 randomized subjects in the Phase 3 MOVe-OUT trial (NCT04575597). MOVe-OUT is a randomized, placebo-controlled, double-blind clinical trial studying LAGEVRIO for the treatment of non-hospitalized patients with mild-to-moderate COVID-19 who are at risk for progressing to severe COVID-19 and/or hospitalization. Eligible subjects were 18 years of age and older and had one or more pre-defined risk factors for disease progression: over 60 years of age, diabetes, obesity (BMI ≥30), chronic kidney disease, serious heart conditions, chronic obstructive pulmonary disease, or active cancer. The study included symptomatic subjects not vaccinated against SARS-CoV-2 and who had laboratory confirmed SARS-CoV-2 infection and symptom onset within 5 days of randomization. Subjects were randomized 1:1 to receive 800 mg of LAGEVRIO or placebo orally twice daily for 5 days.

At baseline, in all randomized subjects, the median age was 43 years (range:18 to 90); 17% of subjects were over 60 years of age and 3% were 75 years of age or older; 49% of subjects were male; 57% were White, 5% Black or African American, 3% Asian, 50% Hispanic or Latino. The majority of subjects were enrolled from sites in Latin America (46%) and Europe (33%); 12% were enrolled in Africa, 6% were enrolled in North America and 3% were enrolled in Asia. Forty-eight percent of subjects received LAGEVRIO or placebo within 3 days of COVID-19 symptom onset. The most common risk factors were obesity (74%), over 60 years of age (17%), and diabetes (16%). Among 792 subjects (55% of total randomized population) with available baseline SARS-CoV-2 variant/clade identification results, 58% were infected with Delta (B.1.617.2 and AY lineages), 20% were infected with Mu (B.1.621), 11% were infected with Gamma (P.1), and the remainder were infected with other variants/clades. Overall, baseline demographic and disease characteristics were well balanced between the treatment arms.

Table 3 provides the results of the primary endpoint (the percentage of subjects who were hospitalized or died through Day 29 due to any cause). The efficacy results are based on unvaccinated adults who were 18 years of age and older and had one or more pre-defined risk factors for disease progression: over 60 years of age, diabetes, obesity (BMI ≥30), chronic kidney disease, serious heart conditions, chronic obstructive pulmonary disease, or active cancer. Please refer to Figure 1 for results by certain subgroups. These subgroup analyses are considered exploratory. Data are not available in certain subgroups of subjects who are at high risk for progression to severe COVID-19 as defined by CDC.

Table 3. Efficacy Results in Non-Hospitalized Adults with COVID-19 [The determination of primary efficacy was based on a planned interim analysis of 762 subjects. At the interim analysis, 7.3% of patients who received LAGEVRIO were either hospitalized or died through Day 29 (28/385), compared with 14.1% of placebo-treated patients (53/377). The adjusted risk difference was -6.8% with a 95% CI of (-11.3%, -2.4%) and 2-sided p-value = 0.0024.]
LAGEVRIO (N=709) n (%) | Placebo (N=699) n (%) | Adjusted Risk Difference % (95% CI)
All-cause hospitalization ≥24 hours for acute care or death through Day 29
48 (6.8%) | 68 (9.7%) | -3.0% (-5.9%, -0.1%)
All-cause mortality through Day 29
1 (0.1%) | 9 (1.3%)
Adjusted relative risk reduction of LAGEVRIO compared to placebo for all randomized subjects was 30% (95% CI: 1%, 51%).
Analyses are adjusted by the stratification factor of time of COVID-19 symptom onset (≤3 days vs. >3 [4-5] days).

Figure 1. Subgroup Efficacy Results in Non-Hospitalized Adults with COVID-19 - All-Randomized Subjects

The corresponding confidence interval is based on Miettinen & Nurminen method.

The modified intent-to-treat population is the efficacy analysis population.

Baseline serum samples were evaluated with the Roche Elecsys anti-N assay to test for the presence of antibodies (IgM, IgG and IgA) against the SARS-CoV-2 nucleocapsid protein.

The findings of these subgroup analyses are considered exploratory.

16 HOW SUPPLIED/STORAGE AND HANDLING

How Supplied

LAGEVRIO capsules are supplied as follows:

Contents | Description | How Supplied | NDC
200 mg molnupiravir | Swedish Orange opaque capsules with corporate logo and “82” printed in white ink | 40 count bottles | NDC-0006-5055-06 NDC-0006-5055-07 NDC-0006-5055-09

Storage and Handling

Store LAGEVRIO capsules at 20° to 25°C (68° to 77°F); excursions permitted between 15° to 30°C (59° to 86°F) [see USP Controlled Room Temperature].

17 PATIENT COUNSELING INFORMATION

As a prescribing healthcare practitioner, you must communicate to the patient and/or caregiver information consistent with the “FACT SHEET FOR PATIENTS AND CAREGIVERS” and document that information was provided. A copy of this Fact Sheet should be provided to the patient and/or caregiver prior to receiving LAGEVRIO [see Box].

Hypersensitivity Reactions

Inform patients that hypersensitivity reactions have been reported, even following a single dose of LAGEVRIO, and to discontinue the drug and to inform their healthcare provider at the first sign of a skin rash, hives or other skin reactions, a rapid heartbeat, difficulty in swallowing or breathing, any swelling suggesting angioedema (for example, swelling of the lips, tongue, face, tightness of the throat, hoarseness), or other symptoms of an allergic reaction [see Warnings and Precautions (5.2)].

Risk of Fetal Toxicity

Advise patients that LAGEVRIO is not recommended for use in pregnancy because it may cause fetal harm. Advise individuals of childbearing potential to inform their healthcare provider of a known or suspected pregnancy [see Box, Warnings and Precautions (5.1) and Use in Specific Populations (8.1)].

Advise individuals of childbearing potential to use effective contraception correctly and consistently while taking LAGEVRIO and for 4 days after the last dose.

While the risk is regarded as low, there is a theoretical risk for LAGEVRIO to affect offspring of treated males based on its mechanism of action. Advise sexually active individuals with partners of childbearing potential to use a reliable method of contraception correctly and consistently while taking LAGEVRIO and for at least 3 months after the last dose of LAGEVRIO. The risk beyond 3 months after the last dose of LAGEVRIO is unknown [see Use in Specific Populations (8.3)].

Risk of Bone and Cartilage Toxicity

LAGEVRIO is not authorized for use in patients less than 18 year of age as it may affect bone growth and cartilage formation [see Warnings and Precautions (5.3) and Use in Specific Populations (8.4)].

Pregnancy Registry

There is a pregnancy registry that monitors pregnancy outcomes in individuals exposed to LAGEVRIO during pregnancy. Encourage participation and advise patients about how they may enroll in the pregnancy registry at https://covid-pr.pregistry.com or 1-800-616-3791 [see Use in Specific Populations (8.1)].

Lactation

Breastfeeding is not recommended while taking LAGEVRIO and for 4 days after the last dose of LAGEVRIO. Advise lactating individuals to consider interrupting breastfeeding and to consider pumping and discarding breast milk during treatment and for 4 days after the last dose of LAGEVRIO [see Use in Specific Populations (8.2)].

Administration Instructions

Inform patients to take LAGEVRIO with or without food. Advise patients to swallow LAGEVRIO capsules whole, and to not open, break, or crush the capsules. Instruct patients that if they miss a dose of LAGEVRIO and it is within 10 hours of the time it is usually taken, the patient should take it as soon as possible and resume the normal dosing schedule. If the patient misses a dose by more than 10 hours, the patient should not take the missed dose and instead take the next dose at the regularly scheduled time. Advise the patient to not double the dose to make up for a missed dose [see Dosage and Administration (2.2)].

LAGEVRIO capsule contents can be mixed with water and given via NG/OG, G and GJ tubes. Inform patients to follow the instructions as described in the fact sheet for patients and caregivers [see Dosage and Administration (2.3)].

Alert the patient of the importance of completing the full 5-day treatment course and to continuing isolation in accordance with public health recommendations to maximize viral clearance and minimize transmission of SARS-CoV-2 [see Dosage and Administration (2.1)].

18 MANUFACTURER INFORMATION

For additional information visit: www.molnupiravir.com

If you have questions, please contact
1-800-672-6372

Manuf. for: Merck Sharp & Dohme LLC
Rahway, NJ 07065, USA

For patent information: www.msd.com/research/patent
Copyright © 2021-2024 Merck & Co., Inc., Rahway, NJ, USA and its affiliates.
All rights reserved.
usfshcp-mk4482-c-2406r010

Fact Sheet for Patients and Caregivers
Emergency Use Authorization (EUA) Of LAGEVRIO™ (molnupiravir) capsules For Coronavirus Disease 2019 (COVID-19)

What is the most important information I should know about LAGEVRIO?

LAGEVRIO may cause serious side effects, including:

- LAGEVRIO may cause harm to your unborn baby. It is not known if LAGEVRIO will harm your baby if you take LAGEVRIO during pregnancy.
  - LAGEVRIO is not recommended for use in pregnancy.
  - LAGEVRIO has not been studied in pregnancy. LAGEVRIO was studied in pregnant animals only. When LAGEVRIO was given to pregnant animals, LAGEVRIO caused harm to their unborn babies.
  - You and your healthcare provider may decide that you should take LAGEVRIO during pregnancy if there are no other COVID-19 treatment options approved or authorized by the FDA that are accessible or clinically appropriate for you.
  - If you and your healthcare provider decide that you should take LAGEVRIO during pregnancy, you and your healthcare provider should discuss the known and potential benefits and the potential risks of taking LAGEVRIO during pregnancy.

For individuals who are able to become pregnant:

- You should use a reliable method of birth control (contraception) correctly and consistently during treatment with LAGEVRIO and for 4 days after the last dose of LAGEVRIO. Talk to your healthcare provider about reliable birth control methods.
- Before starting treatment with LAGEVRIO your healthcare provider may do a pregnancy test to see if you are pregnant before starting treatment with LAGEVRIO.
- Tell your healthcare provider right away if you become pregnant or think you may be pregnant during treatment with LAGEVRIO.

Pregnancy Registry:

- There is a pregnancy registry for individuals who take LAGEVRIO during pregnancy. The purpose of this program is to collect information about the health of you and your baby.
- If you are pregnant or become pregnant during treatment with LAGEVRIO, you are encouraged to report your use of LAGEVRIO during pregnancy to this pregnancy registry at https://covid-pr.pregistry.com or 1-800-616-3791.

For individuals who are sexually active with partners who are able to become pregnant:

- It is not known if LAGEVRIO can affect sperm, but the risk is regarded as low based on animal studies.
- You should use a reliable method of birth control (contraception) correctly and consistently during treatment with LAGEVRIO and for at least 3 months after the last dose. Talk to your healthcare provider about reliable birth control methods.
- The risk to sperm beyond 3 months is not known. Talk to your healthcare provider if you have questions or concerns about how LAGEVRIO may affect sperm.

You are being given this fact sheet because your healthcare provider believes it is necessary to provide you with LAGEVRIO for the treatment of adults with mild-to-moderate coronavirus disease 2019 (COVID-19) who are at high risk for progression to severe COVID-19, including hospitalization or death, and for whom other COVID-19 treatment options approved or authorized by the FDA are not accessible or clinically appropriate.

The U.S. Food and Drug Administration (FDA) has issued an Emergency Use Authorization (EUA) to make LAGEVRIO available during the COVID-19 pandemic (for more details about an EUA please see “What is an Emergency Use Authorization?” at the end of this document). LAGEVRIO is not an FDA-approved medicine in the United States. Read this Fact Sheet for information about LAGEVRIO. Talk to your healthcare provider about your options if you have any questions. It is your choice to take LAGEVRIO.

What is COVID-19?

COVID-19 is caused by a virus called a coronavirus. You can get COVID-19 through close contact with another person who has the virus.

COVID-19 illnesses have ranged from very mild-to-severe, including illness resulting in death. While information so far suggests that most COVID-19 illness is mild, serious illness can happen and may cause some of your other medical conditions to become worse. Older people and people of all ages with severe, long lasting (chronic) medical conditions like heart disease, lung disease and diabetes, for example seem to be at higher risk of being hospitalized for COVID-19.

What is LAGEVRIO?

LAGEVRIO is an investigational medicine used to treat adults with mild to moderate COVID-19:

- who are at high risk for progression to severe COVID-19 including hospitalization or death, and for
- whom other COVID-19 treatment options approved or authorized by the FDA are not accessible or clinically appropriate.

The FDA has authorized the emergency use of LAGEVRIO for the treatment of mild-to-moderate COVID-19 in adults under an EUA. For more information on EUA, see the “What is an Emergency Use Authorization (EUA)?” section at the end of this Fact Sheet.

LAGEVRIO is not authorized:

- for use in people less than 18 years of age.
- for prevention of COVID-19.
- for people needing hospitalization for COVID-19.
- for use for longer than 5 consecutive days.

What should I tell my healthcare provider before I take LAGEVRIO?

Tell your healthcare provider if you:

- have any allergies
- are breastfeeding or plan to breastfeed
- have any serious illnesses
- take any medicines including prescription, over-the-counter medicines, vitamins, and herbal products.

How do I take LAGEVRIO?

- Take LAGEVRIO exactly as your healthcare provider tells you to take it.
- Take 4 capsules of LAGEVRIO every 12 hours (for example, at 8 am and at 8 pm)
- Take LAGEVRIO for 5 days. It is important that you complete the full 5 days of treatment with LAGEVRIO. Do not stop taking LAGEVRIO before you complete the full 5 days of treatment, even if you feel better.
- Take LAGEVRIO with or without food.
- You should stay in isolation for as long as your healthcare provider tells you to. Talk to your healthcare provider if you are not sure about how to properly isolate while you have COVID-19.
- Swallow LAGEVRIO capsules whole. Do not open, break, or crush the capsules. If you cannot swallow capsules whole, tell your healthcare provider.
- If your healthcare provider prescribes LAGEVRIO and tells you to take or give a dose through a nasogastric (NG), orogastric (OG), gastrostomy (G) or gastrojejunostomy (GJ) feeding tube, follow the instructions below: “How to take or give a dose of LAGEVRIO through a nasogastric (NG), orogastric (OG), gastrostomy (G) or gastrojejunostomy (GJ) feeding tube.” You must have an NG, OG, or G feeding tube that is size 12 French or larger, or a GJ feeding tube that is 14 French or larger.
- If you miss a dose of LAGEVRIO:
  - If it has been less than 10 hours since the missed dose, take it as soon as you remember.
  - If it has been more than 10 hours since the missed dose, skip the missed dose and take your dose at the next scheduled time.
- Do not double the dose of LAGEVRIO to make up for a missed dose.

How to take or give a dose of LAGEVRIO through a nasogastric (NG), orogastric (OG), gastrostomy (G) or gastrojejunostomy (GJ) feeding tube:

- Wash your hands well with soap and water.
- Gather the supplies you will need to take or give the prescribed dose of LAGEVRIO.
  - 4 LAGEVRIO capsules
  - 1 liquid measuring cup with mL markings to measure 40 mL of room temperature water
  - 1 clean container with a lid
  - 1 syringe. Your healthcare provider should tell you what size syringe you will need to take or give a dose of LAGEVRIO.
- Place the needed supplies on a clean work surface.
- Follow your healthcare provider’s instructions on how to flush the feeding tube. Flush the feeding tube with 5 mL of water before taking or giving a dose of LAGEVRIO.
- Carefully open 4 LAGEVRIO capsules, one at a time, and empty the contents into a clean container. Discard (throw away) the capsules shells in the household trash.
- Use the liquid measuring cup to measure 40 mL of room temperature water and add to the container containing the capsule contents.
- Place the lid on the container. Shake to mix the capsule contents and water well for 3 minutes. The capsule contents may not dissolve completely.
- Remove the lid from the container and draw up all the LAGEVRIO and water mixture into a syringe.
- Give all of the mixture right away through the feeding tube. If using a GJ tube, give the mixture through the gastric port. Do not keep the mixture for future use.
- If any capsule contents are left in the container:
  - Add 10 mL of water to the container and mix to loosen any capsule contents that are left in the container.
  - Use the syringe to draw up all of the mixture in the container.
  - Give the mixture through the feeding tube.
  - Repeat this process as needed until you no longer see any capsule contents left in the container or syringe.
- Use the same syringe to flush the feeding tube 2 times with 5 mL of water (10 mL total).
- Rinse the container, lid and syringe well with clean water after use. Place on a clean paper towel until next use.

What are the important possible side effects of LAGEVRIO?

- See, “What is the most important information I should know about LAGEVRIO?”
- Allergic Reactions. Allergic reactions can happen in people taking LAGEVRIO, even after only 1 dose. Stop taking LAGEVRIO and call your healthcare provider right away if you get any of the following symptoms of an allergic reaction:
  - hives
  - rapid heartbeat
  - trouble swallowing or breathing
  - swelling of the mouth, lips, or face
  - throat tightness
  - hoarseness
  - skin rash

The most common side effects of LAGEVRIO are:

- diarrhea
- nausea
- dizziness

These are not all the possible side effects of LAGEVRIO. Not many people have taken LAGEVRIO. Serious and unexpected side effects may happen. This medicine is still being studied, so it is possible that all of the risks are not known at this time.

What other treatment choices are there?

Veklury (remdesivir) is FDA-approved as an intravenous (IV) infusion for the treatment of mild-to-moderate COVID-19 in certain adults and children. Paxlovid (nirmatrelvir/ritonavir) is FDA-approved as tablets for the treatment of mild-to-moderate COVID-19 in certain adults. Talk with your doctor to see if Veklury or Paxlovid are appropriate for you.

Like LAGEVRIO, FDA may also allow for the emergency use of other medicines to treat people with COVID-19. Go to https://www.fda.gov/emergency-preparedness-and-response/mcm-legal-regulatory-and-policy-framework/emergency-use-authorization for more information.

It is your choice to be treated or not to be treated with LAGEVRIO. Should you decide not to take it, it will not change your standard medical care.

What if I am breastfeeding?

Breastfeeding is not recommended during treatment with LAGEVRIO and for 4 days after the last dose of LAGEVRIO. If you are breastfeeding or plan to breastfeed, talk to your healthcare provider about your options and specific situation before taking LAGEVRIO.

How do I report side effects with LAGEVRIO?

Contact your healthcare provider if you have any side effects that bother you or do not go away.

Report side effects to FDA MedWatch at www.fda.gov/medwatch or call 1-800-FDA-1088 (1-800-332-1088).

How should I store LAGEVRIO?

- Store LAGEVRIO capsules at room temperature between 68°F to 77°F (20°C to 25°C).
- Keep LAGEVRIO and all medicines out of the reach of children.

How can I learn more about COVID-19?

- Ask your healthcare provider.
- Visit www.cdc.gov/COVID19.
- Contact your local or state public health department.
- Call Merck Sharp & Dohme at 1-800-672-6372 (toll free in the U.S.)
- Visit www.molnupiravir.com.

What Is an Emergency Use Authorization (EUA)?

The United States FDA has made LAGEVRIO available under an emergency access mechanism called an Emergency Use Authorization (EUA) The EUA is supported by a Secretary of Health and Human Service (HHS) declaration that circumstances exist to justify emergency use of drugs and biological products during the COVID-19 pandemic.
LAGEVRIO is authorized for emergency use for the treatment of adults with mild-to-moderate COVID-19 who are at high risk for progression to severe COVID-19, including hospitalization or death, and for whom alternative COVID-19 treatment options approved or authorized by FDA are not accessible or clinically appropriate.

LAGEVRIO as a treatment for COVID-19, has not undergone the same type of review as an FDA-approved product. The FDA may issue an EUA when certain criteria are met, which includes that there are no adequate, approved, and available alternatives. In addition, the FDA decision is based on the totality of scientific evidence available showing that it is reasonable to believe that the product meets certain criteria for safety, performance, and labeling and may be effective in treatment of patients during the COVID-19 pandemic.

All of these criteria must be met to allow for the product to be used in the treatment of patients during the COVID-19 pandemic. The EUA for LAGEVRIO is in effect for the duration of the COVID-19 declaration justifying emergency use of LAGEVRIO, unless terminated or revoked (after which LAGEVRIO may no longer be used under the EUA).

Manuf. for: Merck Sharp & Dohme LLC
Rahway, NJ 07065, USA

For patent information: www.msd.com/research/patent
Copyright © 2021-2024 Merck & Co., Inc., Rahway, NJ, USA and its affiliates.
All rights reserved.

usfsp-mk4482-c-2406r006

Revised: June 2024

PRINCIPAL DISPLAY PANEL - 200 mg Capsules Bottle Label

NDC 0006-5055-06

Lagevrio™
(molnupiravir) capsules

200 mg

For use under Emergency
Use Authorization (EUA)

Each capsule contains 200 mg molnupiravir.

Store at 20°C to 25°C (68°F to 77°F), excursions
permitted to 15°C to 30°C (59°F to 86°F).

Dispense in original container.

Scan QR code or go to www.molnupiravir.com
to access the
FDA-authorized
Fact Sheet for dosage
and administration.

Rx only
40 Capsules